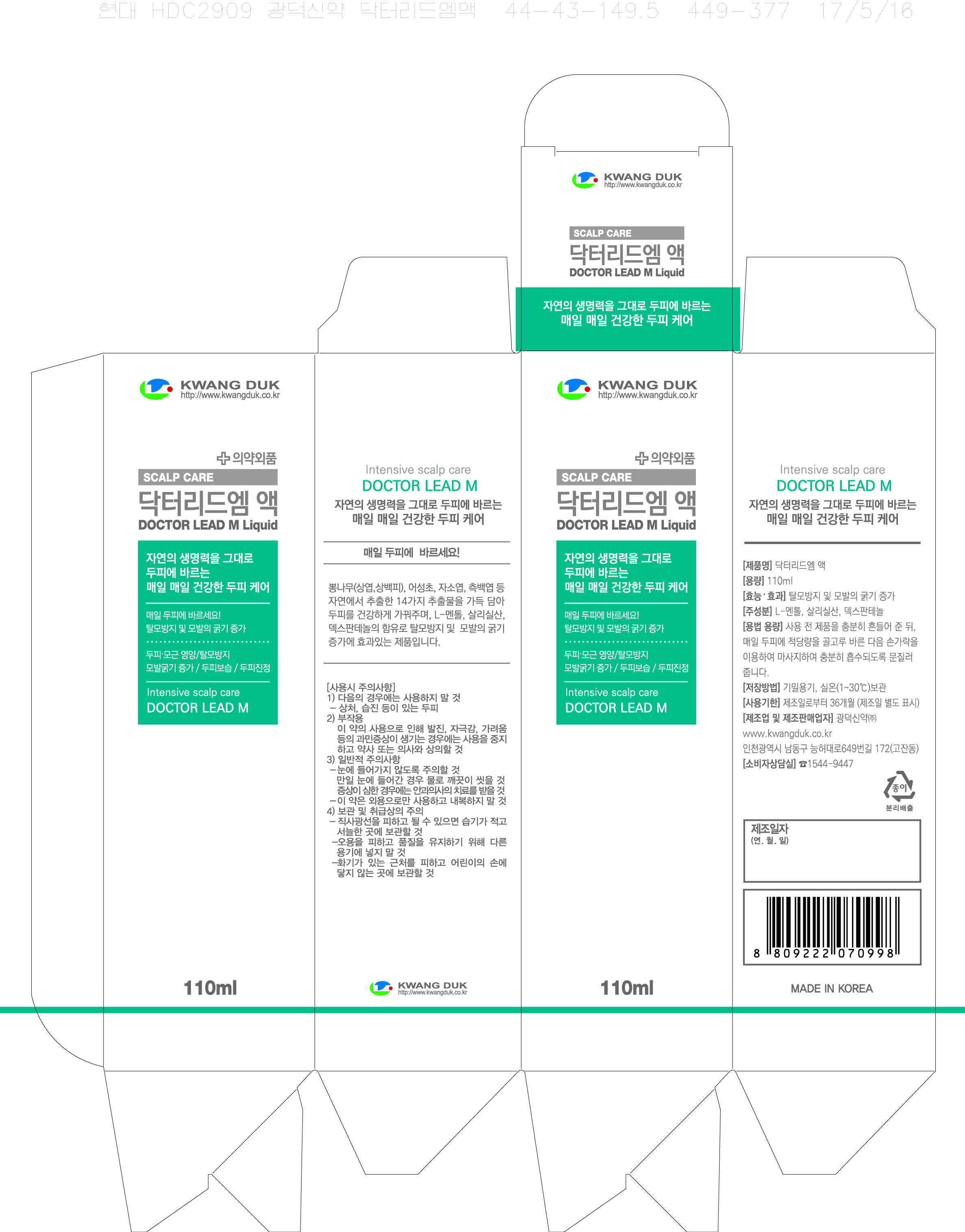 DRUG LABEL: DOCTOR LEAD M
NDC: 71838-0001 | Form: LIQUID
Manufacturer: Kwang Duk Sin Yak Co., Ltd.
Category: otc | Type: HUMAN OTC DRUG LABEL
Date: 20191202

ACTIVE INGREDIENTS: SALICYLIC ACID 25 g/100 mL
INACTIVE INGREDIENTS: PANTHENOL; JOJOBA OIL

Drug Facts

ACTIVE INGREDIENT

salicylic acid

INACTIVE INGREDIENT

panthenol, morus alba bark ext, morus alba leaf ext, alcohol, citric acid, jojoba oil, etc

PURPOSE

Prevents hair loss, thickens hair root and enables improvement on your scalp.

keep out of reach of the children

INDICATIONS AND USAGE

After thoroughly shaking the product before use, apply the appropriate amount to the scalp every day, then massage it with your fingers and rub thoroughly to absorb.

WARNINGS

Cautions :

1. When you use this product and find any of following problems, stop using it. if you keep using it despite the problem, the symptom will get worse, so you will have to go see a dermatologist.

- During use, if you have red spots, swelling, itching, or any other stimuli.

- if the applied region has any problem above for direct light.

2. Do not use the product on wound or dermatitis. 3.Attentive points for storage and treatment :

- Store it in the place where infants or children cannot touch

- do not store it where it has either high or low temperature or there is direct light.

DOSAGE AND ADMINISTRATION

for external use only